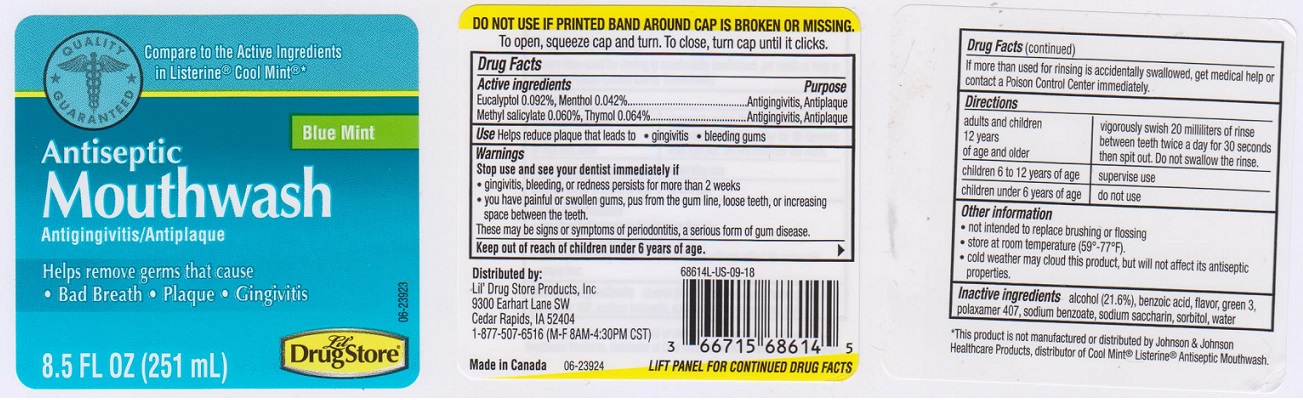 DRUG LABEL: Antiseptic Blue Mint
NDC: 66715-5570 | Form: MOUTHWASH
Manufacturer: LIL' DRUG STORE PRODUCTS, INC.
Category: otc | Type: HUMAN OTC DRUG LABEL
Date: 20190108

ACTIVE INGREDIENTS: EUCALYPTOL 0.92 mg/1 mL; MENTHOL 0.42 mg/1 mL; METHYL SALICYLATE 0.60 mg/1 mL; THYMOL 0.64 mg/1 mL
INACTIVE INGREDIENTS: WATER; ALCOHOL; BENZOIC ACID; FD&C GREEN NO. 3; POLOXAMER 407; SODIUM BENZOATE; SACCHARIN SODIUM; SORBITOL

Drug Facts

Active ingredients

Eucalyptol 0.092%, Menthol 0.042%, Methyl Salicylate 0.060%, Thymol 0.064%

Purpose

Antigingivitis/Antiplaque

Uses

Helps reduce plaque that leads to

- gingivitis
- bleeding gums

Warnings

Stop use and see your dentist immediately if

- gingivitis, bleeding, or redness persists for more than 2 weeks
- you have painful or swollen gums, pus from the gum line, loose teeth, or increasing space between the teeth. These may be signs or symptoms or periodontitis, a serious form of gum disease

Keep out of reach of children.

If more than used for rinsing is accidentally swallowed, get medical help or contact a Poison Control Center immediately.

Directions

- Adults and children 12 years of age and older: vigorously swish 20 milliliters of rinse between teeth twice a day for 30 seconds then spit out. Do not swallow the rinse.

- Children 6 to 12 years of age: supervise use

- Children under 6 years of age: do not use

Other information

- not intended to replace brushing or flossing
- store at room temperature (59°F - 77°F)
- cold weather may cloud this product, but will not affect its antiseptic properties

Inactive ingredients

alcohol (21.6%), benzoic acid, flavor, green 3, poloxamer 407, sodium benzoate, sodium saccharin, sorbitol, water.